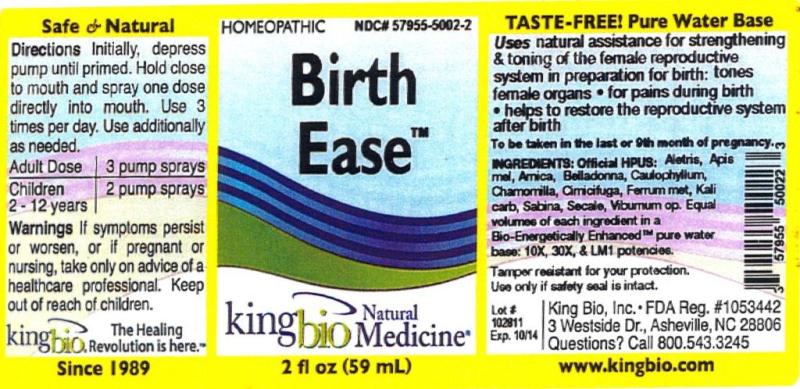 DRUG LABEL: Birth Ease
NDC: 57955-5002 | Form: LIQUID
Manufacturer: King Bio, Inc.
Category: homeopathic | Type: HUMAN OTC DRUG LABEL
Date: 20120619

ACTIVE INGREDIENTS: ALETRIS FARINOSA ROOT 10 [hp_X]/59 mL; APIS MELLIFERA 10 [hp_X]/59 mL; ARNICA MONTANA 10 [hp_X]/59 mL; ATROPA BELLADONNA 10 [hp_X]/59 mL; CAULOPHYLLUM THALICTROIDES ROOT 10 [hp_X]/59 mL; MATRICARIA RECUTITA 10 [hp_X]/59 mL; BLACK COHOSH 10 [hp_X]/59 mL; IRON 10 [hp_X]/59 mL; POTASSIUM CARBONATE 10 [hp_X]/59 mL; JUNIPERUS SABINA LEAFY TWIG 10 [hp_X]/59 mL; CLAVICEPS PURPUREA SCLEROTIUM 10 [hp_X]/59 mL; VIBURNUM OPULUS BARK 10 [hp_X]/59 mL
INACTIVE INGREDIENTS: WATER

Birth Ease

Active Ingredients

Official HPUS: Aletris farinosa, Apis mellifica, Arnica montana, Belladonna, Caulophyllum thalictroides, Chamomilla, Cimicifuga racemosa, Ferrum metallicum, Kali carbonicum, Sabina, Secale cornutum, Viburnum opulus.

Reference image: birthease.jpg

Inactive Ingredient

Equal volumes of each ingredient in a Bio-Energetically Enhanced pure water base: 10X, 30X, and LM1 potencies.

Reference image: birthease.jpg

Purposes

Uses natural assistance for strengthening and toning of the female reproductive system in preparation for birth:

- tones female organs
- for pains during birth
- helps to restore the reproductive system after birth

To be taken in the last or 9th month of pregnancy.
Reference image: birthease.jpg

Dosage and Administration

Directions: Initially, depress pump until primed. Hold close to mouth and spray one dose directly into mouth. Use 3 times per day. Use additionally as needed.

Adult Dose - 3 pump sprays

Children 2-12 years - 2 pump sprays

Reference image: birthease.jpg

Warnings

If symptoms persist or worsen, or if pregnant or nursing, take only on advice of a healthcare professional. Keep out of reach of children.

Tamper resistant for your protection. Use only if safety seal is intact.

Reference image: birthease.jpg

Keep out of reach of children.

Reference image: birthease.jpg

Indications and Usage

Natural assistance for strengthening and toning of the female reproductive system in preparations for birth: tones female organs, for pains during birth, helps to restore the reproductive system after birth. To be taken in the last or 9th month of pregnancy.
Reference image: birthease.jpg

PACKAGE LABEL

King Bio, Inc.

3 Westside Dr.

Asheville, NC 28806

Questions? Call 800.543.3245

www.kingbio.com